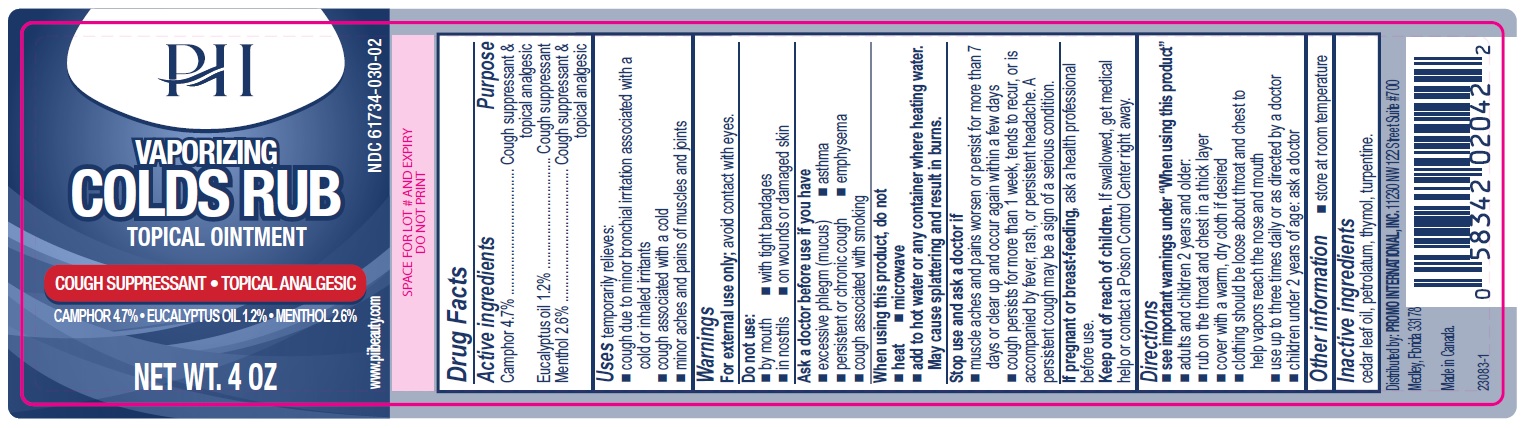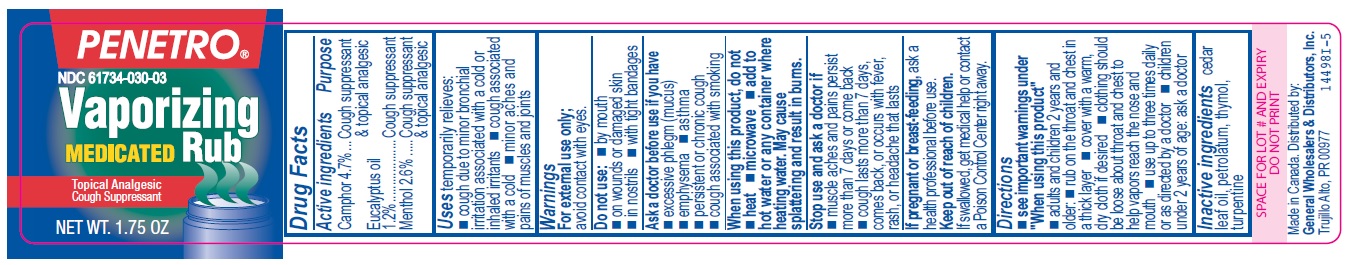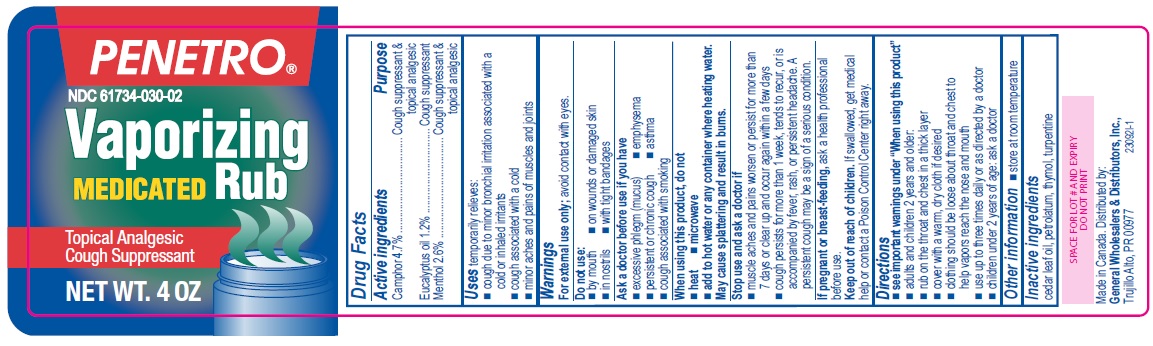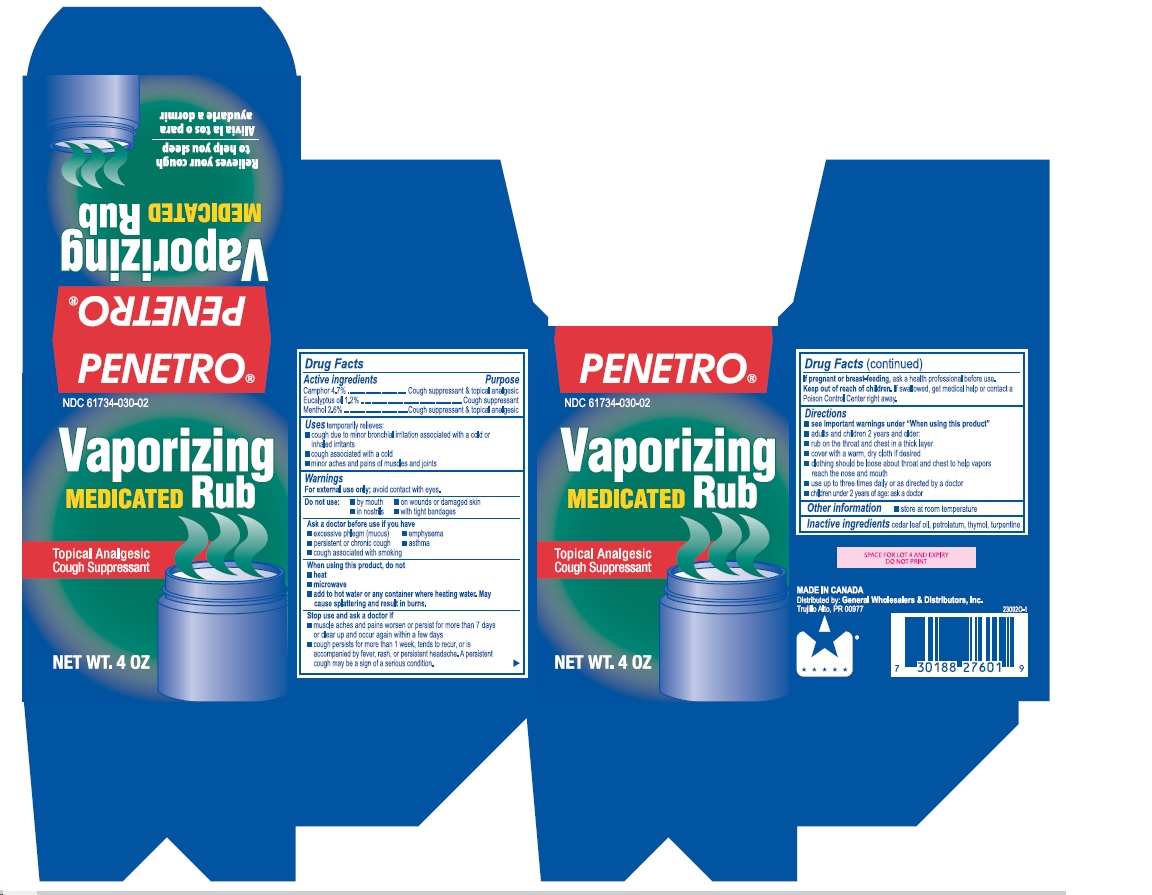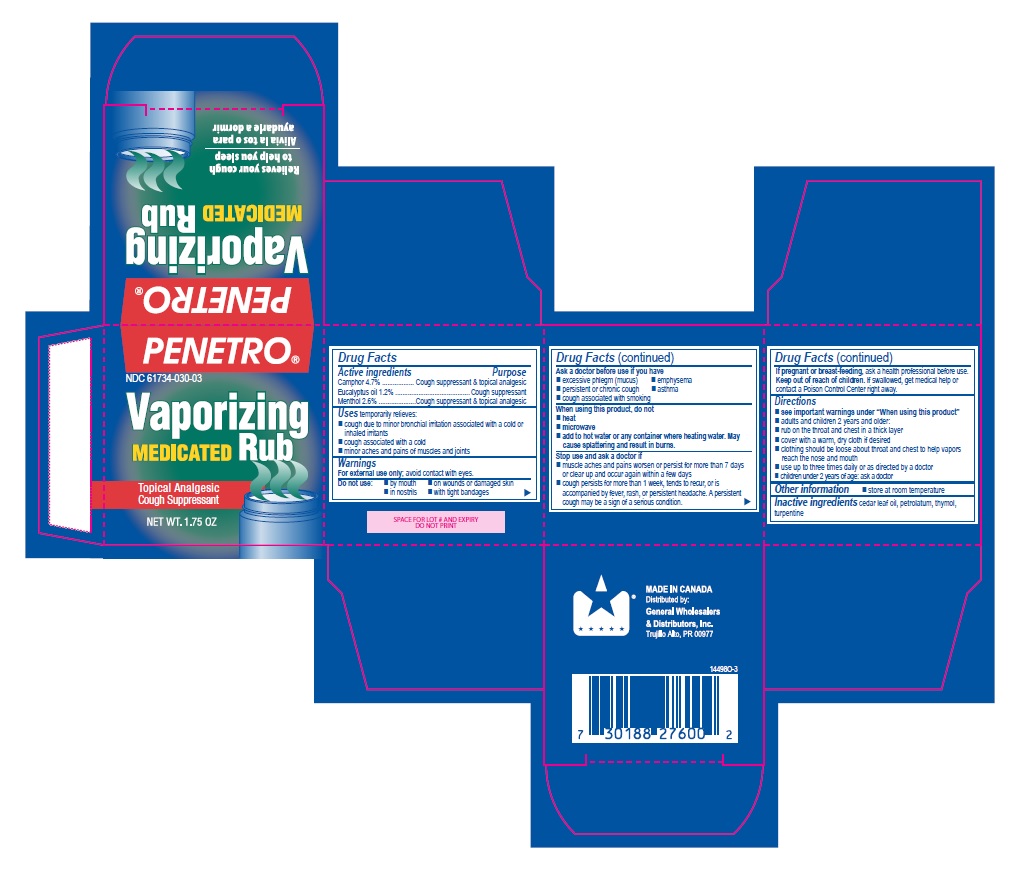 DRUG LABEL: Vaporizing Colds Rub
NDC: 61734-030 | Form: OINTMENT
Manufacturer: Delon Laboratories (1990) Ltd
Category: otc | Type: HUMAN OTC DRUG LABEL
Date: 20251016

ACTIVE INGREDIENTS: MENTHOL 2.6 g/100 g; EUCALYPTUS OIL 1.2 g/100 g; CAMPHOR (SYNTHETIC) 4.73 g/100 g
INACTIVE INGREDIENTS: PETROLATUM; CEDAR LEAF OIL; THYMOL; TURPENTINE

Vaporizing Cold Rub

Active ingredients

Camphor 4.7%
Eucalyptus oil 1.2%
Menthol 2.6%

Purpose

Cough suppressant & topical analgesic

Cough suppressant

Cough suppressant & topical analgesic

Uses

temporarily relieves:

- cough due to minor bronchial irritation associated with a cold or inhaled irritants
- cough associated with a cold
- minor aches and pains of muscles and joints

Warnings

For external use only; avoid contact with eyes.

Do not use:

- by mouth
- on wounds or damaged skin
- in nostrils
- with tight bandages

Ask a doctor before use if you have

- excessive phlegm (mucus)
- emphysema
- persistent or chronic cough
- asthma
- cough associated with smoking

When using this product, do not

- heat
- microwave
- add to hot water or any container where heating water. May cause splattering and result in burns.

Stop use and ask a doctor if

- muscle aches and pains worsen or persist for more than 7 days or clear up and occur again within a few days
- cough perists for more than 1 week, tends to recur, or is accompanied by fever, rash, or persistent headache. A persistent cough may be a sign of a serious condition.

PREGNANCY OR BREAST FEEDING

If pregnant or breast-feeding, ask a health professional before use.

Keep out of reach of children. If swallowed, get medical help or contact a Poison Control Center right away.

Directions

- see important warnings under "When using this product"
- adults and children 2 years and older:
- rub on the throat and chest in a thick layer
- cover with a warm, dry cloth if desired
- clothing should be loose about throat and chest to help vapors reach the nose and mouth
- use up to three times daily or as directed by a doctor
- children under 2 years of age: ask a doctor

Other information

- store at room temperature

Inactive ingredients

cedar leaf oil, petrolatum, thymol, turpentine